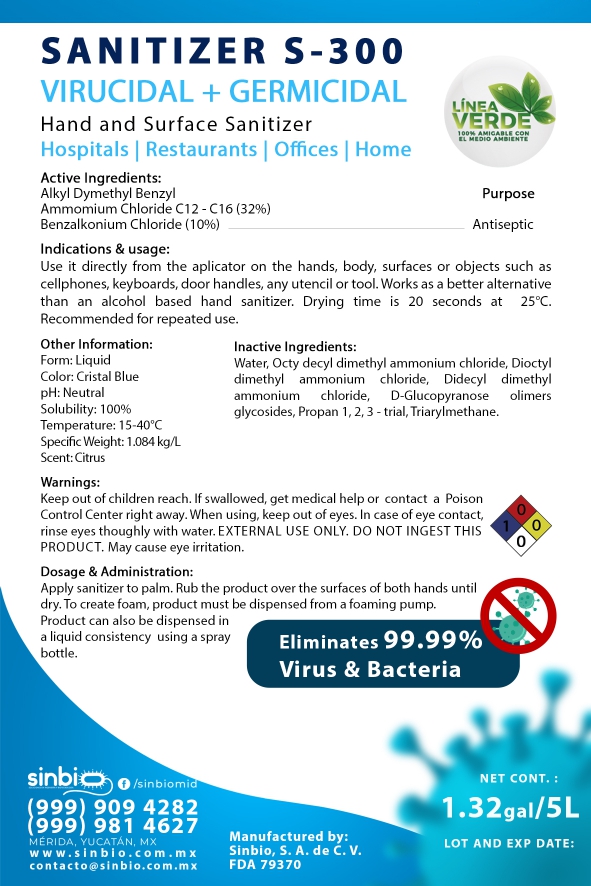 DRUG LABEL: SINBIO Sanitizer S-300
NDC: 79370-001 | Form: LIQUID
Manufacturer: SINBIO, S.A. DE C.V.
Category: otc | Type: HUMAN OTC DRUG LABEL
Date: 20200620

ACTIVE INGREDIENTS: N-ALKYL DIMETHYL BENZYL AMMONIUM CHLORIDE (C12-C18) 0.32 mg/0.001 L; BENZALKONIUM CHLORIDE 0.1 mg/0.001 L
INACTIVE INGREDIENTS: OCTYLDIMETHYLAMMONIUM CHLORIDE; BENZYLDIMETHYLOCTYLAMMONIUM CHLORIDE; WATER; DIDECYLDIMONIUM CHLORIDE; ALCOHOL

DOSAGE & ADMINISTRATION SECTION

79370-001-01

INACTIVE INGREDIENT SECTION

79370-001-01

RECENT MAJOR CHANGES SECTION

79370-001-01

WARNINGS SECTION

79370-001-01

INDICATIONS & USAGE SECTION

79370-001-01

OTC - KEEP OUT OF REACH OF CHILDREN SECTION

79370-001-01

OTC - PURPOSE SECTION

79370-001-01

OTC - ACTIVE INGREDIENT SECTION

79370-001-01

PACKAGE LABEL PRINCIPAL DISPLAY PANEL

79370-001-01